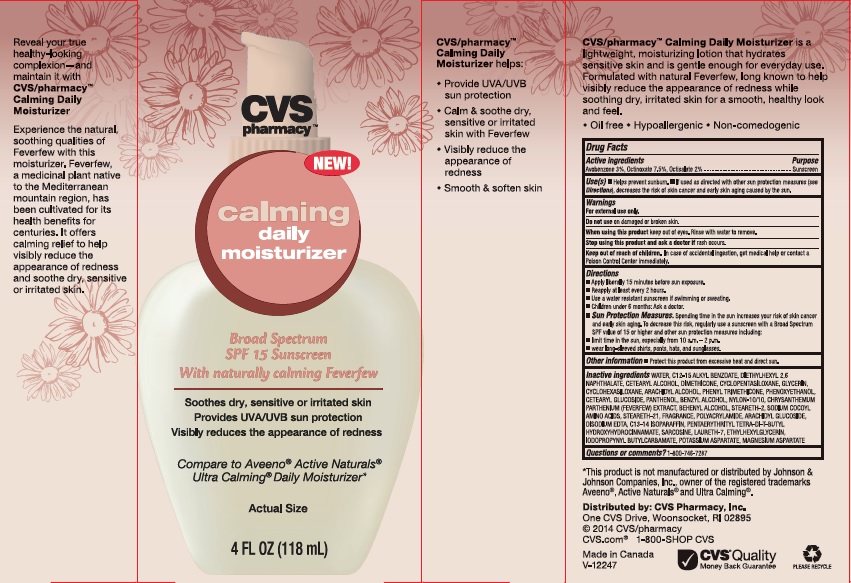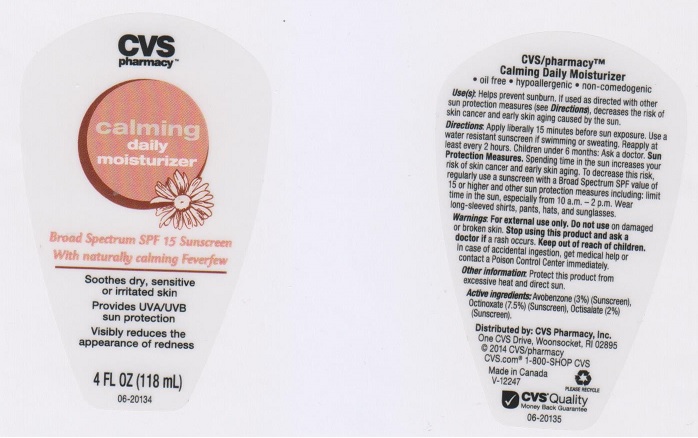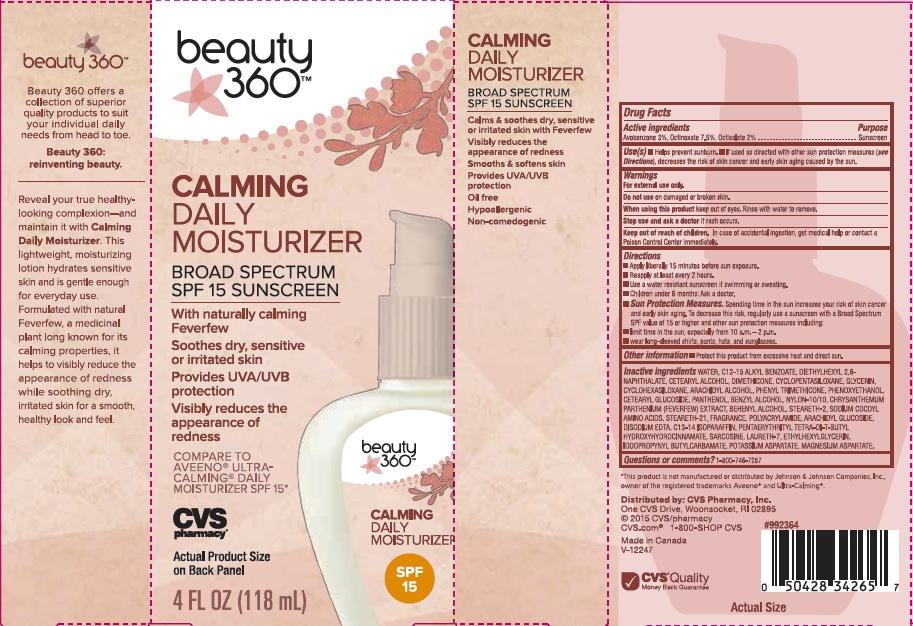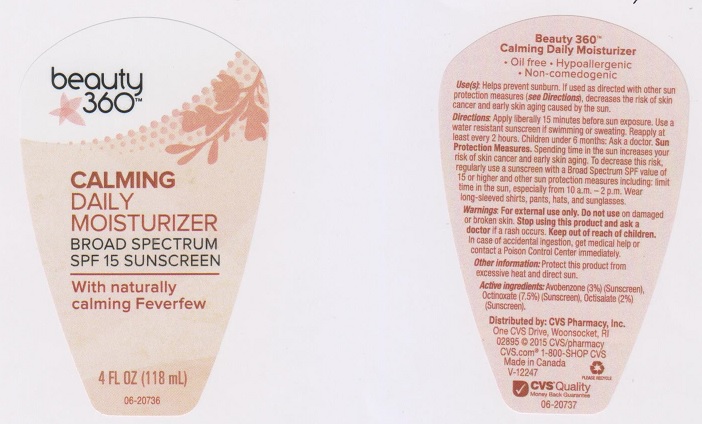 DRUG LABEL: CVS PHARMACY CALMING DAILY MOISTURIZER
NDC: 59779-598 | Form: LOTION
Manufacturer: CVS PHARMACY
Category: otc | Type: HUMAN OTC DRUG LABEL
Date: 20151117

ACTIVE INGREDIENTS: AVOBENZONE 30 mg/1 mL; OCTINOXATE 75 mg/1 mL; OCTISALATE 20 mg/1 mL
INACTIVE INGREDIENTS: WATER; C12-15 ALKYL BENZOATE; DIETHYLHEXYL 2,6-NAPHTHALATE; CETOSTEARYL ALCOHOL; DIMETHICONE; CYCLOMETHICONE 5; GLYCERIN; CYCLOMETHICONE 6; ARACHIDYL ALCOHOL; PHENYL TRIMETHICONE; PHENOXYETHANOL; CETEARYL GLUCOSIDE; PANTHENOL; BENZYL ALCOHOL; NYLON-12; TANACETUM PARTHENIUM; DOCOSANOL; STEARETH-2; STEARETH-21; POLYACRYLAMIDE (10000 MW); ARACHIDYL GLUCOSIDE; EDETATE DISODIUM; C13-14 ISOPARAFFIN; PENTAERYTHRITOL TETRAKIS(3-(3,5-DI-TERT-BUTYL-4-HYDROXYPHENYL)PROPIONATE); SARCOSINE; LAURETH-7; ETHYLHEXYLGLYCERIN; IODOPROPYNYL BUTYLCARBAMATE; POTASSIUM ASPARTATE; MAGNESIUM ASPARTATE

DRUG FACTS

Active ingredients

Avobenzone 3%, Octinoxate 7.5%, Octisalate 2%

Purpose

Sunscreen

Use(s)

- Helps prevent sunburn.
- If used as directed with other sun protection measures (see Directions), decreases the risk of skin cancer and early skin aging caused by the sun.

Warnings

For external use only.

Do not use

on damaged or broken skin.

When using this product

keep out of eyes. Rinse with water to remove.

Stop use and ask a doctor if

rash occurs.

Keep out of reach of children.

In case of accidental ingestion, get medical help or contact a Poison Control Center immediately.

Directions

- Apply liberally 15 minutes before sun exposure.
- Reapply at least every 2 hours.
- Use a water resistant sunscreen if swimming or sweating.
- Children under 6 months: Ask a doctor.
- Sun Protection Measure. Spending time in the sun increases your risk of skin cancer and early skin aging. To decrease this risk, regularly use a sunscreen with a Broad Spectrum SPF value of 15 or higher and other sun protection measures including:
- limit time in the sun, especially from 10 a.m. - 2 p.m.
- wear long-sleeved shirts, pants, hats, and sunglasses.

Other information

Protect this product from excessive heat and direct sun

Inactive ingredients

Water, C12-15 Alkyl Benzoate, Diethylhexyl 2,6-Naphthalate, Cetearyl Alcohol, Dimethicone, Cyclopentasiloxane, Glycerin, Cyclohexasiloxane, Arachidyl Alcohol, Phenyl Trimethicone, Phenoxyethanol, Cetearyl Glucoside, Panthenol, Benzyl Alcohol, Nylon-10/10, Chrysanthemum Parthenium (Feverfew) Extract, Behenyl Alcohol, Steareth-2, Sodium Cocoyl Amino Acids, Steareth-21, Fragrance, Polyacrylamide, Arachidyl Glucoside, Disodium EDTA, C13-14 Isoparaffin, Pentaerythrityl Tetra-di-t-Butyl Hydroxyhydrocinnamate, Sarcosine, Laureth-7, Ethylhexylglycerin, Iodopropynyl Butylcarbamate, Potassium Aspartate, Magnesium Aspartate.

Questions or comments?

1-800-746-7287